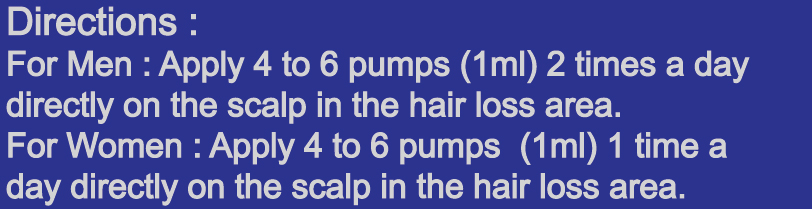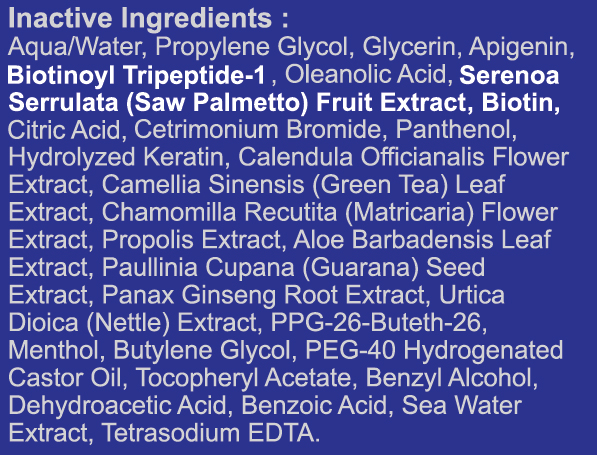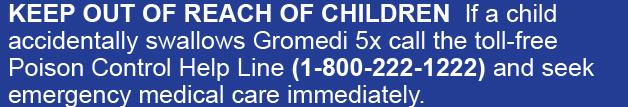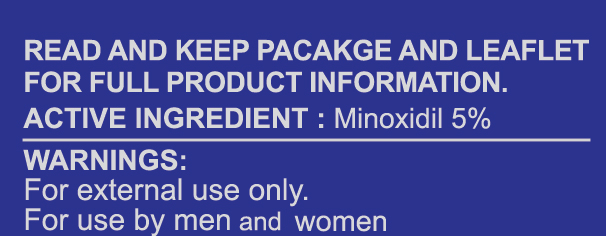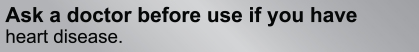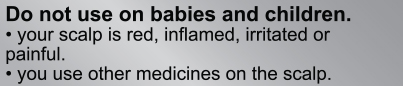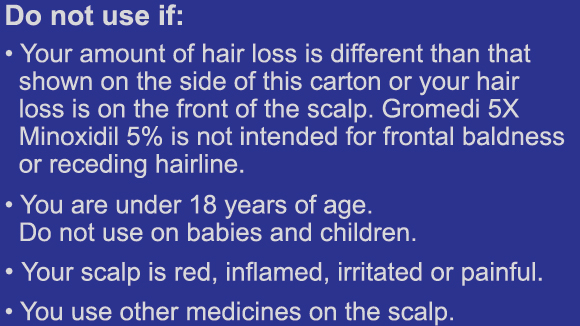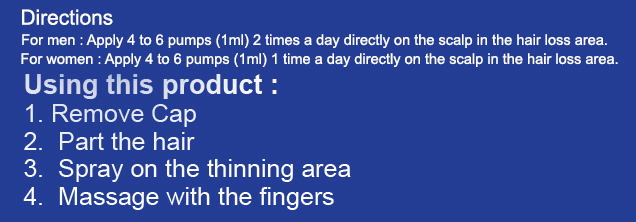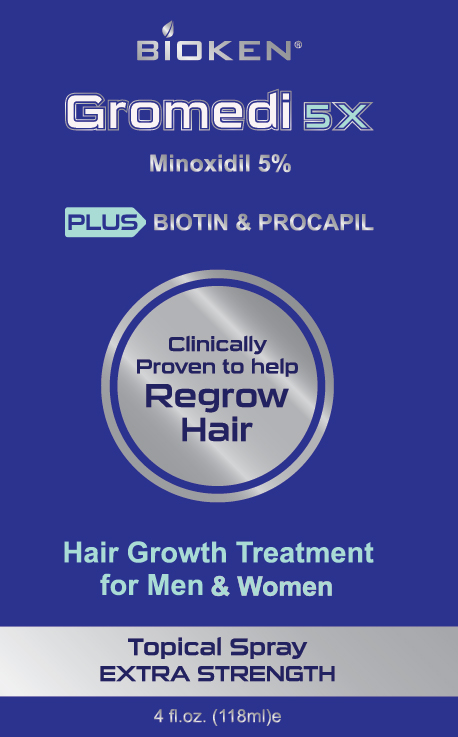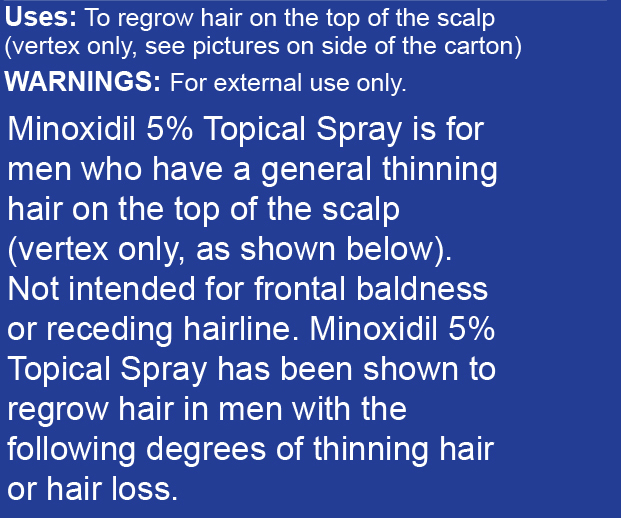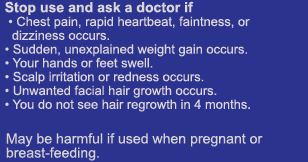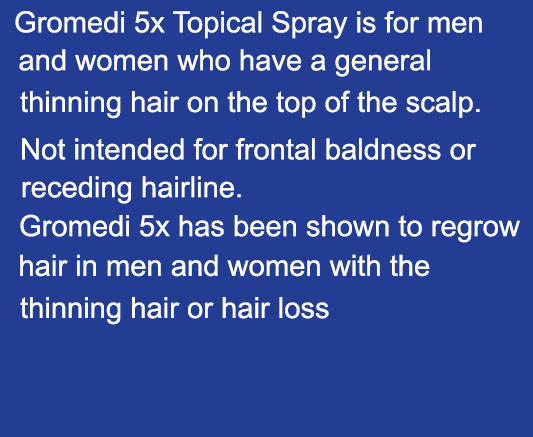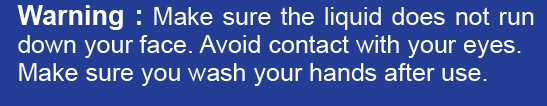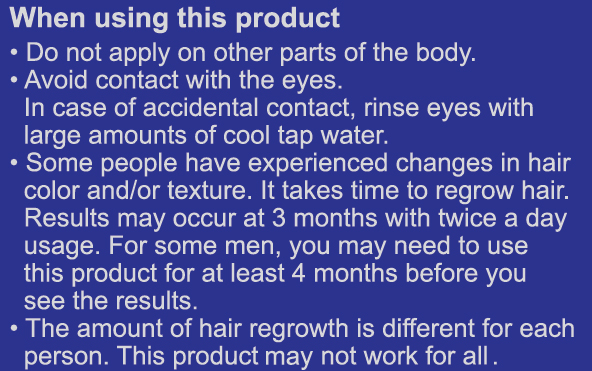 DRUG LABEL: Gromedi 5x
NDC: 71331-104 | Form: SPRAY
Manufacturer: Orange Lab
Category: otc | Type: HUMAN OTC DRUG LABEL
Date: 20181001

ACTIVE INGREDIENTS: MINOXIDIL 5 g/100 g
INACTIVE INGREDIENTS: APIGENIN; BIOTINOYL TRIPEPTIDE-1; SAW PALMETTO; ANHYDROUS CITRIC ACID; OLEANOLIC ACID; PROPYLENE GLYCOL; GLYCERIN; URTICA DIOICA ROOT; PPG-26-BUTETH-26; BUTYLENE GLYCOL; BENZYL ALCOHOL; BENZOIC ACID; EDETATE SODIUM; PANTHENOL; BIOTIN; CALENDULA OFFICINALIS FLOWER; GREEN TEA LEAF; BEE PROPOLIS EXTRACT; PAULLINIA CUPANA SEED; ASIAN GINSENG; MENTHOL; CETRIMONIUM BROMIDE; ALOE VERA LEAF; .ALPHA.-TOCOPHEROL ACETATE, DL-; DEHYDROACETIC ACID

Gromedi 5x Topical Spray